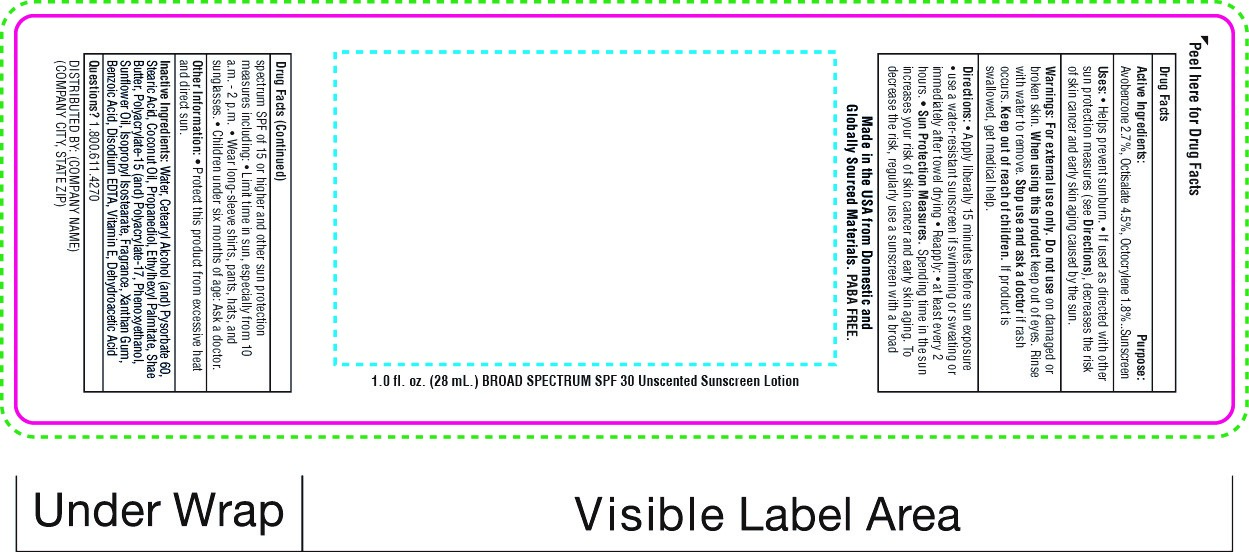 DRUG LABEL: SnugZ SPF 30 Broad Spectrum Sunscreen
NDC: 76309-400 | Form: LOTION
Manufacturer: SnugZ/USA, LLC
Category: otc | Type: HUMAN OTC DRUG LABEL
Date: 20251229

ACTIVE INGREDIENTS: AVOBENZONE 0.000714 mg/28 mL; OCTISALATE 0.00198 mg/28 mL; OCTOCRYLENE 0.0018 mg/28 mL
INACTIVE INGREDIENTS: COCONUT OIL

ZSUN30 - SPF 30 Broad Spectrum Sunscreen Lotion